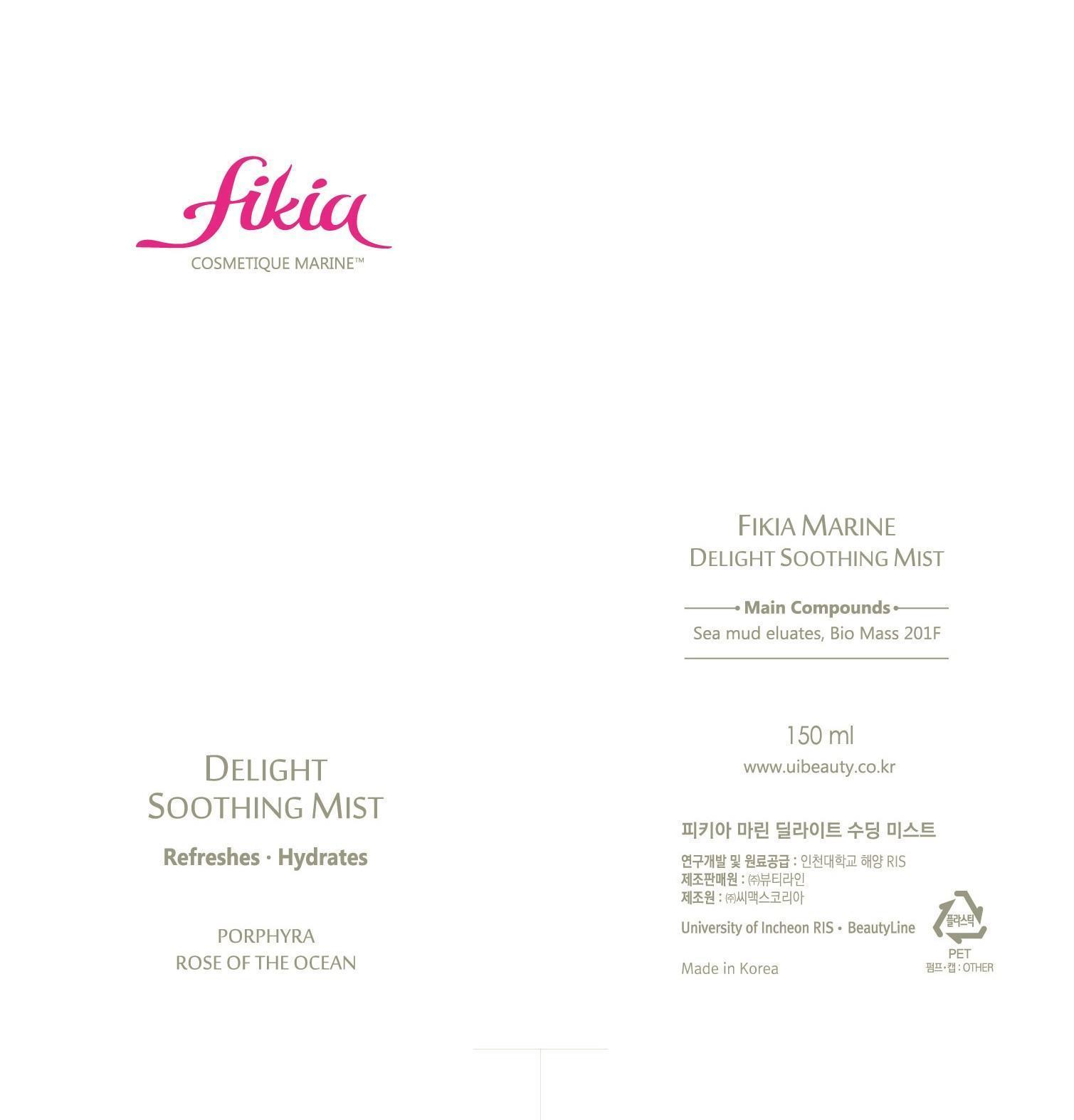 DRUG LABEL: Fikia Marine Delight Soothing Mist
NDC: 69327-2001 | Form: LIQUID
Manufacturer: Beauty Line Co., Ltd.
Category: otc | Type: HUMAN OTC DRUG LABEL
Date: 20141025

ACTIVE INGREDIENTS: ALLANTOIN 0.1 g/100 mL
INACTIVE INGREDIENTS: WATER; BUTYLENE GLYCOL; BETAINE

Drug Facts

ACTIVE INGREDIENT

allantoin

INACTIVE INGREDIENT

water, maris aqua, porphyra tenera ext, butylene glycol, calactomyces ferment filtrate, etc

PURPOSE

instantly dehydrates, leaving the skin soothed

keep out or reach of the children

INDICATIONS AND USAGE

Directions for Use : After cleansing, hold 20~30 cm away from face and spray 3~4 times. Lightly pat to help absorption. To be sprayed whenever skin feel dehydrated. Can also be used in the last stages of make-up.

WARNINGS

1)If in contact with the eyes, wash out thoroughty with water If the symptoms are servere, seek medical advice immediately
2)This product is for exeternal use only. Do not use for internal use
4.Storage and handling precautions
1)If possible, avoid direct sunlight and store in cool and area of low humidity
2)In order to maintain the quality of the product and avoid misuse
3)Avoid placing the product near fire and store out in reach of children

DOSAGE AND ADMINISTRATION

for external use only